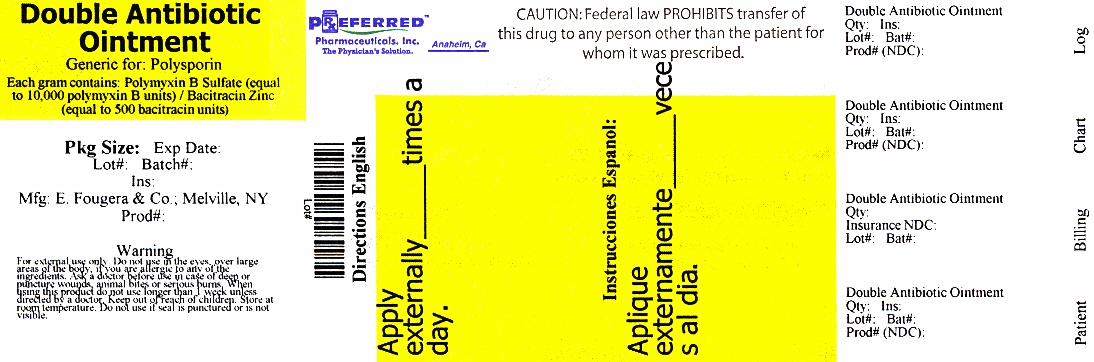 DRUG LABEL: Double Antibiotic
NDC: 68788-9488 | Form: OINTMENT
Manufacturer: Preferred Pharmaceuticals, Inc.
Category: otc | Type: HUMAN OTC DRUG LABEL
Date: 20140522

ACTIVE INGREDIENTS: Bacitracin Zinc 500 [USP'U]/1 g; Polymyxin B Sulfate 10000 [USP'U]/1 g
INACTIVE INGREDIENTS: petrolatum

Fougera ® Double Antibiotic Ointment
(Bacitracin Zinc and Polymyxin B Sulfate Ointment USP)

Active ingredients (in each gram)

Bacitracin Zinc (equal to 500 bacitracin units)

Polymyxin B Sulfate (equal to 10,000 polymyxin B units)

Purpose

Antibiotic

Antibiotic

Uses

first aid to help prevent infection in

- minor cuts
- scrapes
- burn

For external use only

Do not use

- in the eyes
- over large areas of the body
- if you are allergic to any of the ingredients

Ask a doctor before use in case of deep or puncture wounds, animal bites or serious burns

When using this product do not use longer than 1 week unless directed by a doctor

Stop use and ask a doctor if

- the condition persists or gets worse
- if a rash or other allergic reaction develops

Keep out of reach of children.

If swallowed, get medical help or contact a Poison Control Center right away.

Directions

- clean the affected area
- apply a small amount of this product (an amount equal to the surface area of the tip of a finger) on the area 1 to 3 times daily
- may be covered with a sterile bandage

Other information store at room temperature

Inactive ingredient white petrolatum

Questions or comments? call toll free 1-800-645-9833

PACKAGE LABEL – PRINCIPAL DISPLAY PANEL

28gr tube - 68788-9488-2

Fougera ®

Double Antibiotic Ointment
(Bacitracin Zinc and Polymyxin B Sulfate Ointment USP)

First Aid Antibiotic